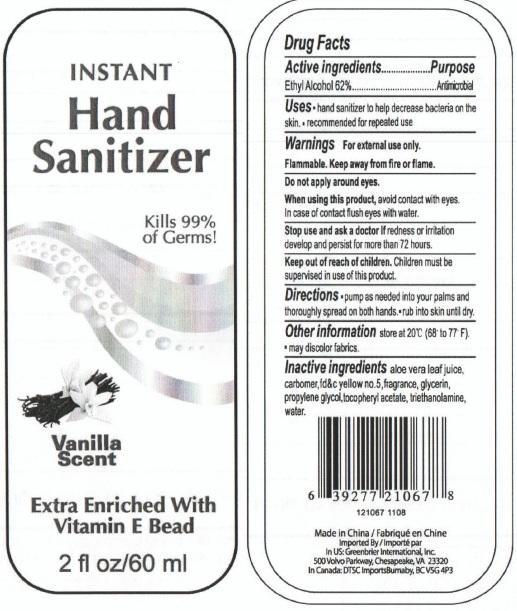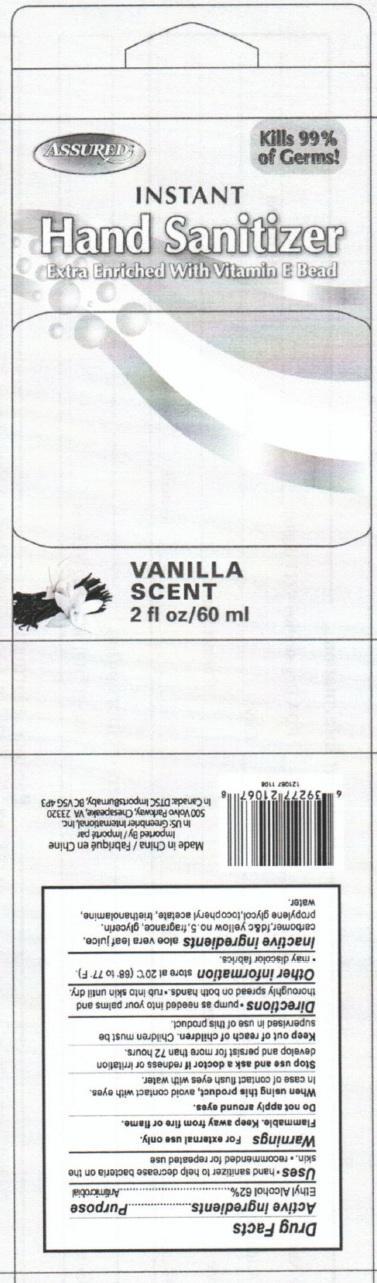 DRUG LABEL: INSTANT Hand Sanitizer Extra Enriched With Vitamin E Vanilla Scent 
NDC: 33992-1067 | Form: GEL
Manufacturer: Greenbrier International, Inc.
Category: otc | Type: HUMAN OTC DRUG LABEL
Date: 20150218

ACTIVE INGREDIENTS: ALCOHOL 62 mL/100 mL
INACTIVE INGREDIENTS: ALOE VERA LEAF; FD&C YELLOW NO. 6; GLYCERIN; PROPYLENE GLYCOL; ALPHA-TOCOPHEROL ACETATE; TROLAMINE

INSTANT Hand Sanitizer Extra Enriched With Vitamin E Bead Vanilla Scent

Drug Facts

Active Ingredients

Ethyl Alcohol 62%

Purpose
Antiseptic

Uses

- Hand sanitizer to help decrease bacteria on the skin.
- When water, soap and towel are not available.
- Recommended for repeated use.

Warnings For external use only.

SAFE HANDLING WARNING

Flammable. Keep away from fire or flame.

WHEN USING

Do not apply around eyes. Do not use in ears and mouth

When using this product, avoid contact with eyes.

In case of contact flush eyes with water.

Stop use and ask a doctor if redness or irritation develop and persist for more than 72 hours.

Keep out of reach of children. Children must be supervised in use of this product.

Directions

- pump as needed into your palms and thoroughly spread on both hands
- rub into skin until dry.

Other Information

store at 20 degrees C (68 to 77 degrees F).

- may discolor fabrics.

Inactive Ingredients

aloe vera leaf juice, carbomer, fd and c yellow no. 5, fragrance, glycerin, propylene glycol, tocopheryl acetate, triethanolamine, water.

DESCRIPTION

This product is not manufactured or distributed by Johnson and Johnson

or McNeil-PPC, Inc. distributor of Purell hand sanitizers.

Distributed By: GREENBRIAR INTERNATIONAL, INC.,

CHESAPEAKE, VA 23320

MADE IN CHINA

PACKAGE LABEL

INSTANT

Hand Sanitizer

with Moisturizers

Kills 99.99 percent of Germs!

Extra Enriched With Vitamin E Bead

Vanilla Scent